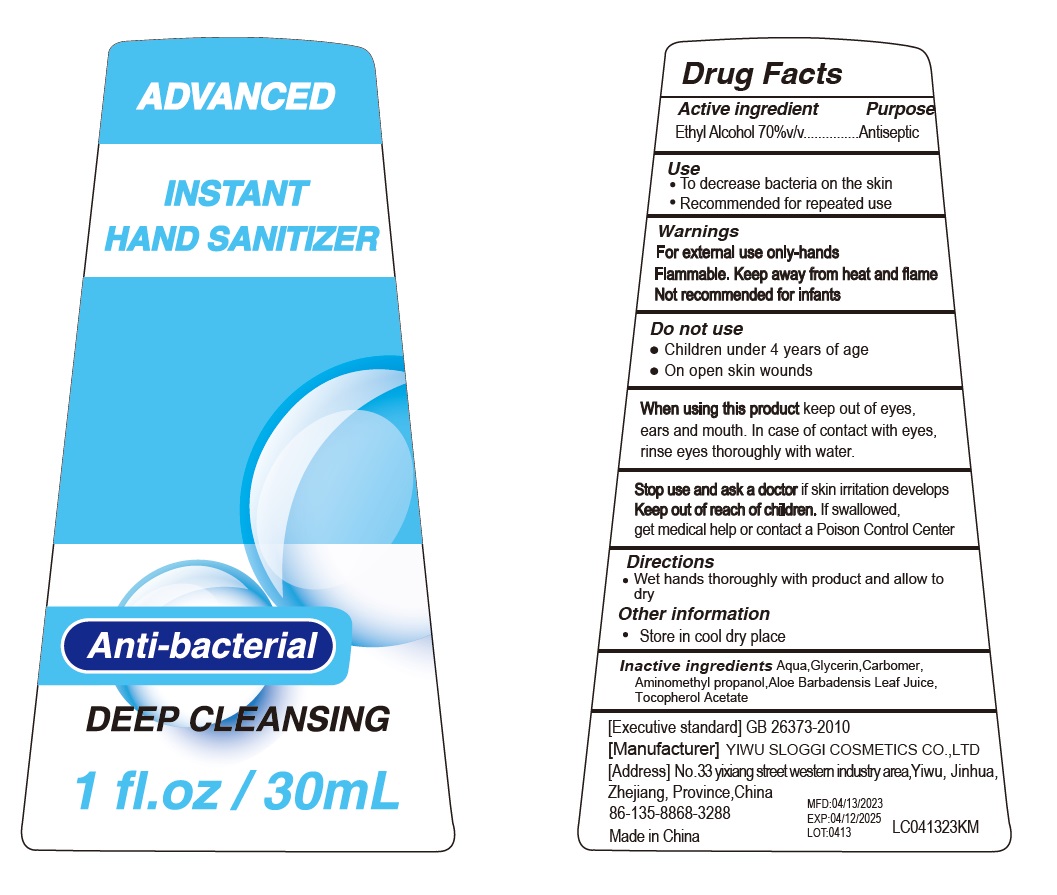 DRUG LABEL: INSTANT HAND SANITIZER
NDC: 54225-013 | Form: GEL
Manufacturer: YIWU SLOGGI COSMETICS CO.,LTD
Category: otc | Type: HUMAN OTC DRUG LABEL
Date: 20230525

ACTIVE INGREDIENTS: ALCOHOL 70 mL/100 mL
INACTIVE INGREDIENTS: .ALPHA.-TOCOPHEROL ACETATE; CARBOMER HOMOPOLYMER, UNSPECIFIED TYPE; GLYCERIN; AMINOMETHYLPROPANOL; WATER; ALOE VERA LEAF

Active ingredients

Ethyl Alcohol 70% v/v

Purpose

Antiseptic

Use

To decrease bacteria on the skin
Recommended for repeated use

Warning

For external use only-hands Flammable.

Keep away from heat and flame

Not recommended for infants

Do not use

Children under 4 years of age

On open skin wounds

When using this product

keep out of eyes, ears and mouth.In case of contact with eyes, rinse eyes thorougly with water.

Stop use and ask doctor

if skin irrtation develops

keep out of reach of children

If swallowed,

get medical help or contact a Poison Control Center

Directions

Wet hands thoroughly with product and allow to dry

Other information

Store in cool dry place

Inactive ingredients

Aqua,Glycerin,Carbomer, Aminomethyl propanol,Aloe Barbadensis Leaf Juice,Tocopherol Acetate